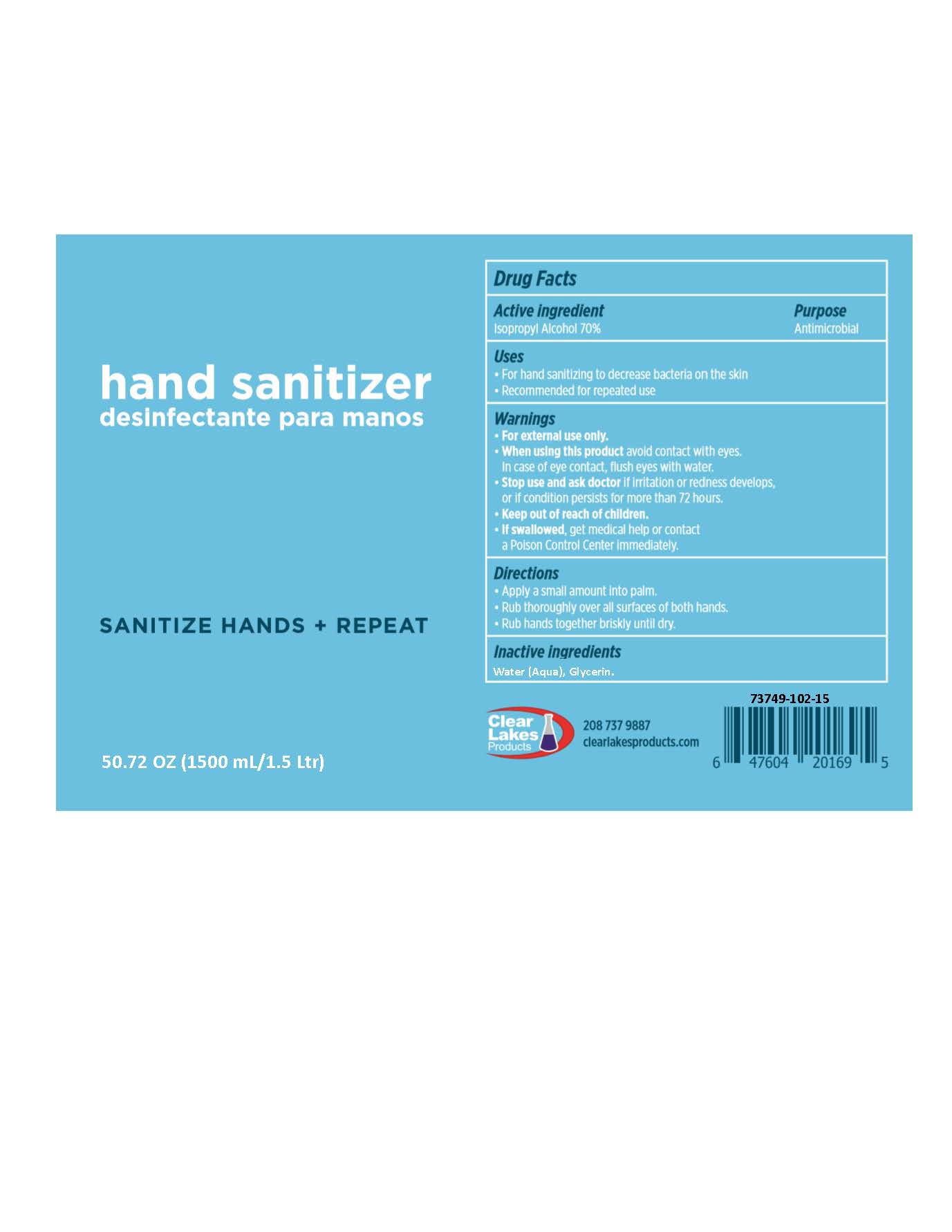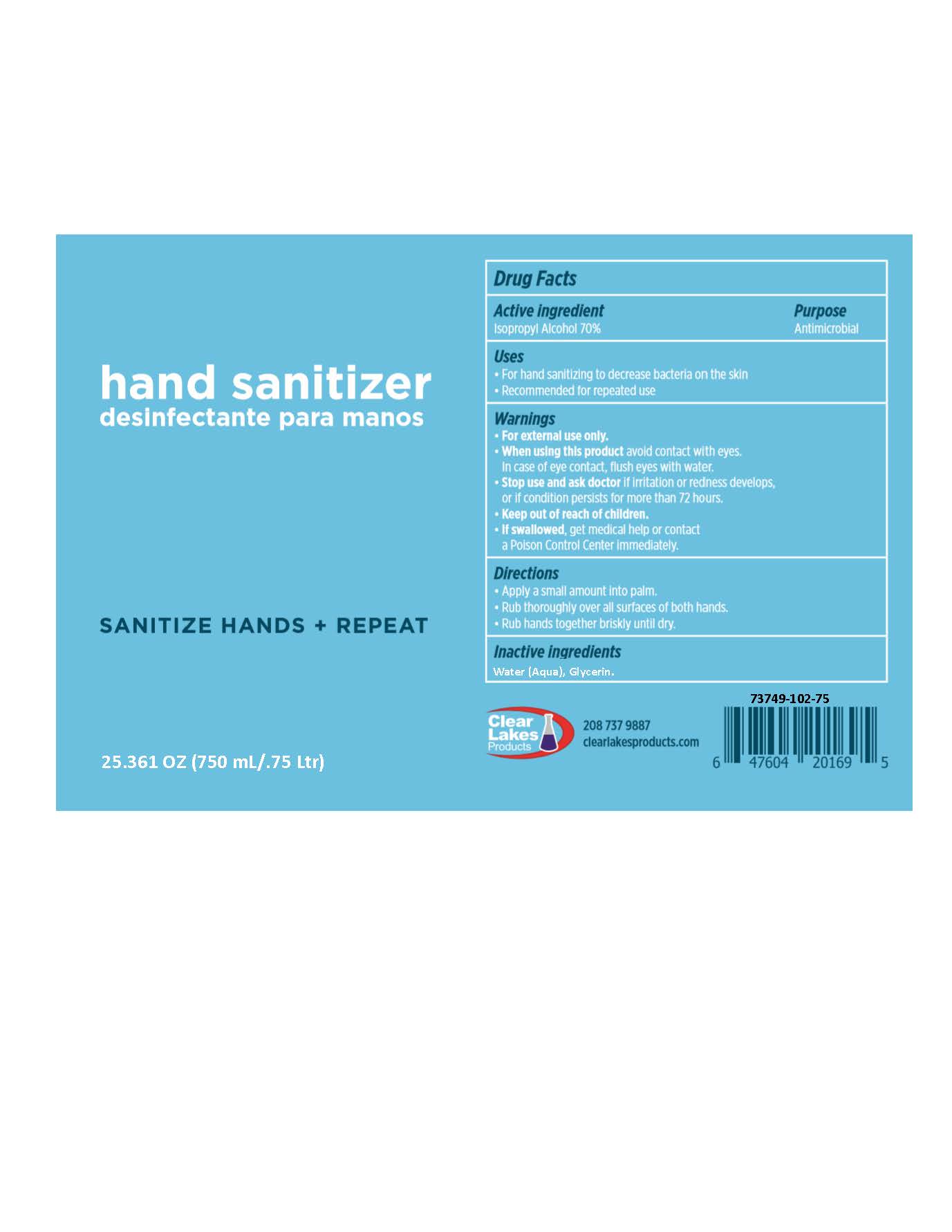 DRUG LABEL: Hand Sanitizer
NDC: 73749-102 | Form: GEL
Manufacturer: Clear Lakes Products, LLC
Category: otc | Type: HUMAN OTC DRUG LABEL
Date: 20201231

ACTIVE INGREDIENTS: ISOPROPYL ALCOHOL 70 mL/100 mL
INACTIVE INGREDIENTS: GLYCERIN; WATER

Active Ingredient(s)

Isopropyl Alcohol 70% Purpose: Antiseptic

Purpose

Antimicrobial

Use

- For hand sanitizing to decrease bacteria on the skin
- Recommended for repeated use

Warnings

For external use only. Flammable. Keep away from heat or flame

When using this product keep out of eyes, ears, and mouth. In case of contact with eyes, rinse eyes thoroughly with water.
Stop use and ask a doctor if irritation or rash occurs. These may be signs of a serious condition.
Keep out of reach of children. If swallowed, get medical help or contact a Poison Control Center right away.

Do not use

- When Using this product avoid contact with eyes. In case of eye contact, flush eyes with water.

Stop use and ask a doctor if irritation or redness develops or if condition persists for more than 72 hours.

Keep out of reach of children. If swallowed, get medical help or contact a Poison Control Center right away.

WARNINGS

If swallowed, get medical help or contact a Poison Control Center immediately.

Directions

- Apply a small amount into palm.
- Rub thoroughly over all surfaces of both hands.
- Rub hands together briskly until dry.

Inactive ingredients

Water (Aqua), Glycerin.

Package Label - Principal Display Panel

1500 ml NDC: 73749-102-15

Package label 750 mL 73749-102-75

750 mL 73749-102-75